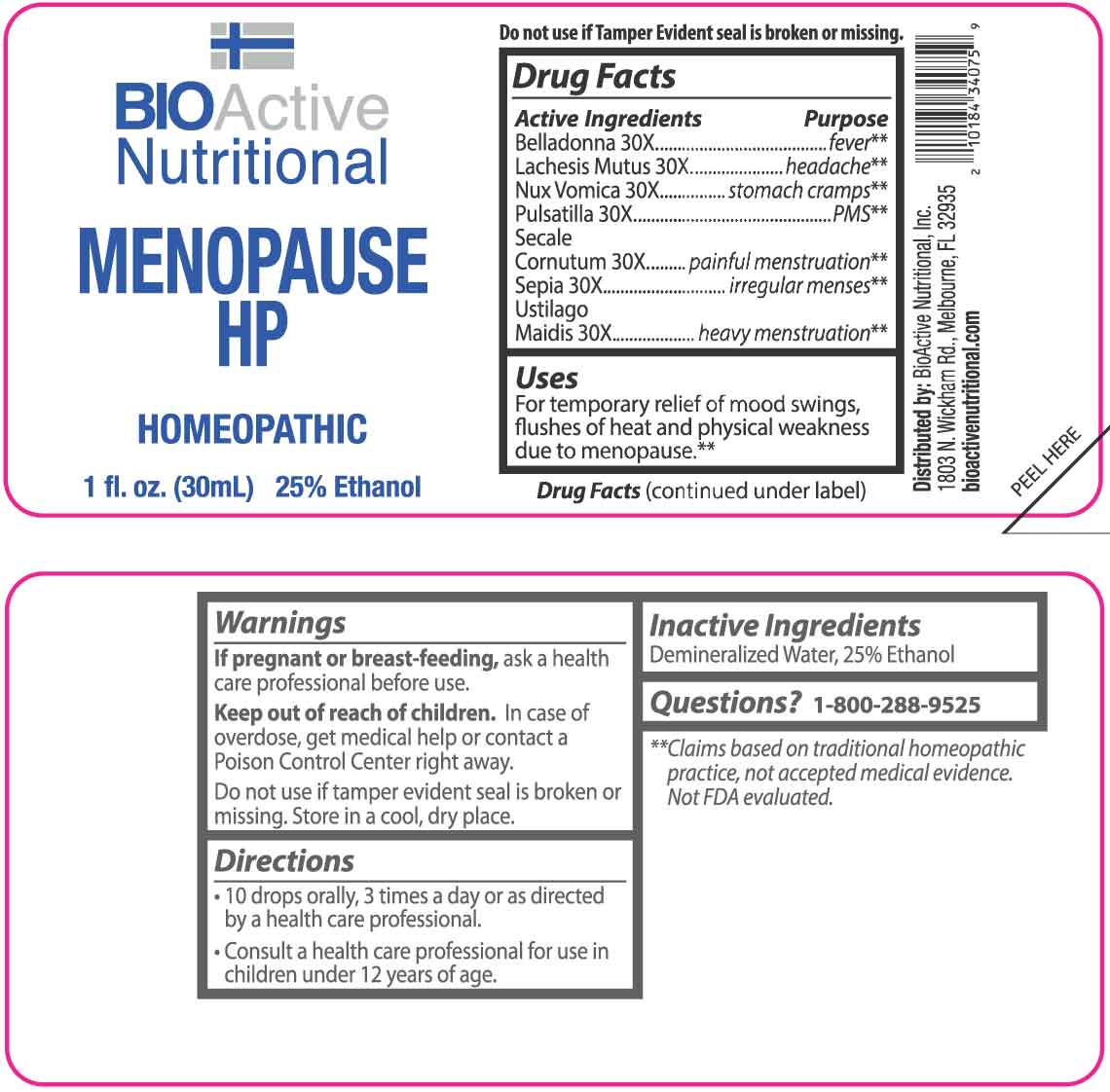 DRUG LABEL: Menopause HP
NDC: 43857-0203 | Form: LIQUID
Manufacturer: BioActive Nutritional, Inc.
Category: homeopathic | Type: HUMAN OTC DRUG LABEL
Date: 20251217

ACTIVE INGREDIENTS: ATROPA BELLADONNA 30 [hp_X]/1 mL; LACHESIS MUTA VENOM 30 [hp_X]/1 mL; STRYCHNOS NUX-VOMICA SEED 30 [hp_X]/1 mL; PULSATILLA VULGARIS WHOLE 30 [hp_X]/1 mL; CLAVICEPS PURPUREA SCLEROTIUM 30 [hp_X]/1 mL; SEPIA OFFICINALIS JUICE 30 [hp_X]/1 mL; USTILAGO MAYDIS 30 [hp_X]/1 mL
INACTIVE INGREDIENTS: WATER; ALCOHOL

DRUG FACTS:

ACTIVE INGREDIENTS:

Belladonna 30X, Lachesis Mutus 30X, Nux Vomica 30X, Pulsatilla 30X, Secale Cornutum 30X, Sepia 30X, Ustilago Maidis 30X.

PURPOSE:

Belladonna - fever,** Lachesis Mutus - headache,** Nux Vomica - stomach cramps,** Pulsatilla - PMS,** Secale Cornutum - painful menstruation,** Sepia - irregular menses,** Ustilago Maidis - heavy menstruation**

**Claims based on traditional homeopathic practice, not accepted medical evidence. Not FDA evaluated.

USES:

For temporary relief of mood swings, flushes of heat and physical weakness due to menopause.**

**Claims based on traditional homeopathic practice, not accepted medical evidence. Not FDA evaluated.

WARNINGS:

If pregnant or breast-feeding, ask a health care professional before use.

Keep out of reach of children. In case of overdose, get medical help or contact a Poison Control Center right away.

Do not use if tamper evident seal is broken or missing.

Store in a cool, dry place.

KEEP OUT OF REACH OF CHILDREN:

In case of overdose, get medical help or contact a Poison Control Center right away.

DIRECTIONS:

• 10 drops orally, 3 times a day or as directed by a health care professional.

• Consult a health care professional for use in children under 12 years of age.

INACTIVE INGREDIENTS:

Demineralized Water, 25% Ethanol

QUESTIONS:

Distributed by:

BIOActive Nutritional, Inc.

1803 N. Wickham Rd.

Melbourne, FL 32935

bioactivenutritional.com

1-800-288-9525

PACKAGE LABEL DISPLAY:

BIOActive Nutritional

MENOPAUSE HP

HOMEOPATHIC

1 fl. oz. (30 mL)